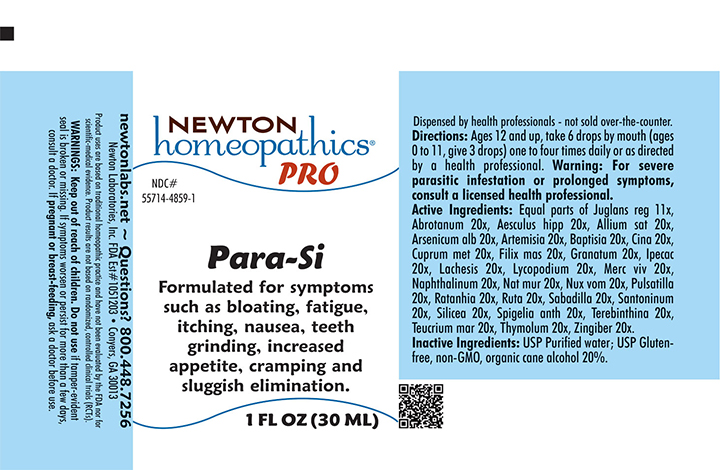 DRUG LABEL: Para-Si
NDC: 55714-4859 | Form: LIQUID
Manufacturer: Newton Laboratories, Inc.
Category: homeopathic | Type: HUMAN OTC DRUG LABEL
Date: 20241126

ACTIVE INGREDIENTS: ARTEMISIA ABROTANUM FLOWERING TOP 20 [hp_X]/1 mL; HORSE CHESTNUT 20 [hp_X]/1 mL; GARLIC 20 [hp_X]/1 mL; ARSENIC TRIOXIDE 20 [hp_X]/1 mL; ARTEMISIA VULGARIS ROOT 20 [hp_X]/1 mL; BAPTISIA TINCTORIA ROOT 20 [hp_X]/1 mL; ARTEMISIA CINA PRE-FLOWERING TOP 20 [hp_X]/1 mL; COPPER 20 [hp_X]/1 mL; DRYOPTERIS FILIX-MAS ROOT 20 [hp_X]/1 mL; PUNICA GRANATUM ROOT BARK 20 [hp_X]/1 mL; IPECAC 20 [hp_X]/1 mL; LACHESIS MUTA VENOM 20 [hp_X]/1 mL; LYCOPODIUM CLAVATUM SPORE 20 [hp_X]/1 mL; MERCURY 20 [hp_X]/1 mL; NAPHTHALENE 20 [hp_X]/1 mL; SODIUM CHLORIDE 20 [hp_X]/1 mL; STRYCHNOS NUX-VOMICA SEED 20 [hp_X]/1 mL; ANEMONE PULSATILLA 20 [hp_X]/1 mL; KRAMERIA LAPPACEA ROOT 20 [hp_X]/1 mL; RUTA GRAVEOLENS FLOWERING TOP 20 [hp_X]/1 mL; SCHOENOCAULON OFFICINALE SEED 20 [hp_X]/1 mL; SANTONIN 20 [hp_X]/1 mL; SILICON DIOXIDE 20 [hp_X]/1 mL; SPIGELIA ANTHELMIA 20 [hp_X]/1 mL; GINGER 20 [hp_X]/1 mL; TURPENTINE OIL 20 [hp_X]/1 mL; TEUCRIUM MARUM 20 [hp_X]/1 mL; THYMOL 20 [hp_X]/1 mL; JUGLANS REGIA LEAF 11 [hp_X]/1 mL
INACTIVE INGREDIENTS: WATER; ALCOHOL

Para-Si 4859L

INDICATIONS & USAGE SECTION

Formulated for symptoms such as bloating, fatigue, itching, nausea, teeth grinding, increased appetite, cramping and sluggish elimination.

DOSAGE & ADMINISTRATION SECTION

Directions: Ages 12 and up, take 6 drops by mouth (ages 0 to 11, give 3 drops) one to four times daily or as directed by a health professional. Warning: For severe parasitic infestation or prolonged symptoms, consult a licensed health professional.

OTC - ACTIVE INGREDIENT SECTION

Equal parts of Juglans reg 11x, Abrotanum 20x, Aesculus hipp 20x, Allium sat 20x, Arsenicum alb 20x, Artemisia 20x, Baptisia 20x, Cina 20x, Cuprum met 20x, Filix mas 20x, Granatum 20x, Ipecac 20x, Lachesis 20x, Lycopodium 20x, Merc viv 20x, Naphthalinum 20x, Nat mur 20x, Nux vom 20x, Pulsatilla 20x, Ratanhia 20x, Ruta 20x, Sabadilla 20x, Santoninum 20x, Silicea 20x, Spigelia anth 20x, Terebinthina 20x, Teucrium mar 20x, Thymolum 20x, Zingiber 20x.

QUESTIONS SECTION

newtonlabs.net - Questions? 800.448.7256

Newton Laboratories, Inc. FDA Est # 1051203 - Conyers, GA 30013

OTC - PURPOSE SECTION

Formulated for symptoms such as bloating, fatigue, itching, nausea, teeth grinding, increased appetite, cramping and sluggish elimination.

INACTIVE INGREDIENT SECTION

Inactive Ingredients: USP Purified Water; USP Gluten-free, non-GMO, organic cane alcohol 20%

WARNINGS SECTION

WARNINGS: Keep out of reach of children. Do not use if tamper-evident seal is broken or missing. If symptoms worsen or persist for more than a few days, consult a doctor. If pregnant or breast-feeding, ask a doctor before use.

OTC - PREGNANCY OR BREAST FEEDING SECTION

If pregnant or breast-feeding, ask a doctor before use.

OTC - KEEP OUT OF REACH OF CHILDREN SECTION

Keep out of reach of children.